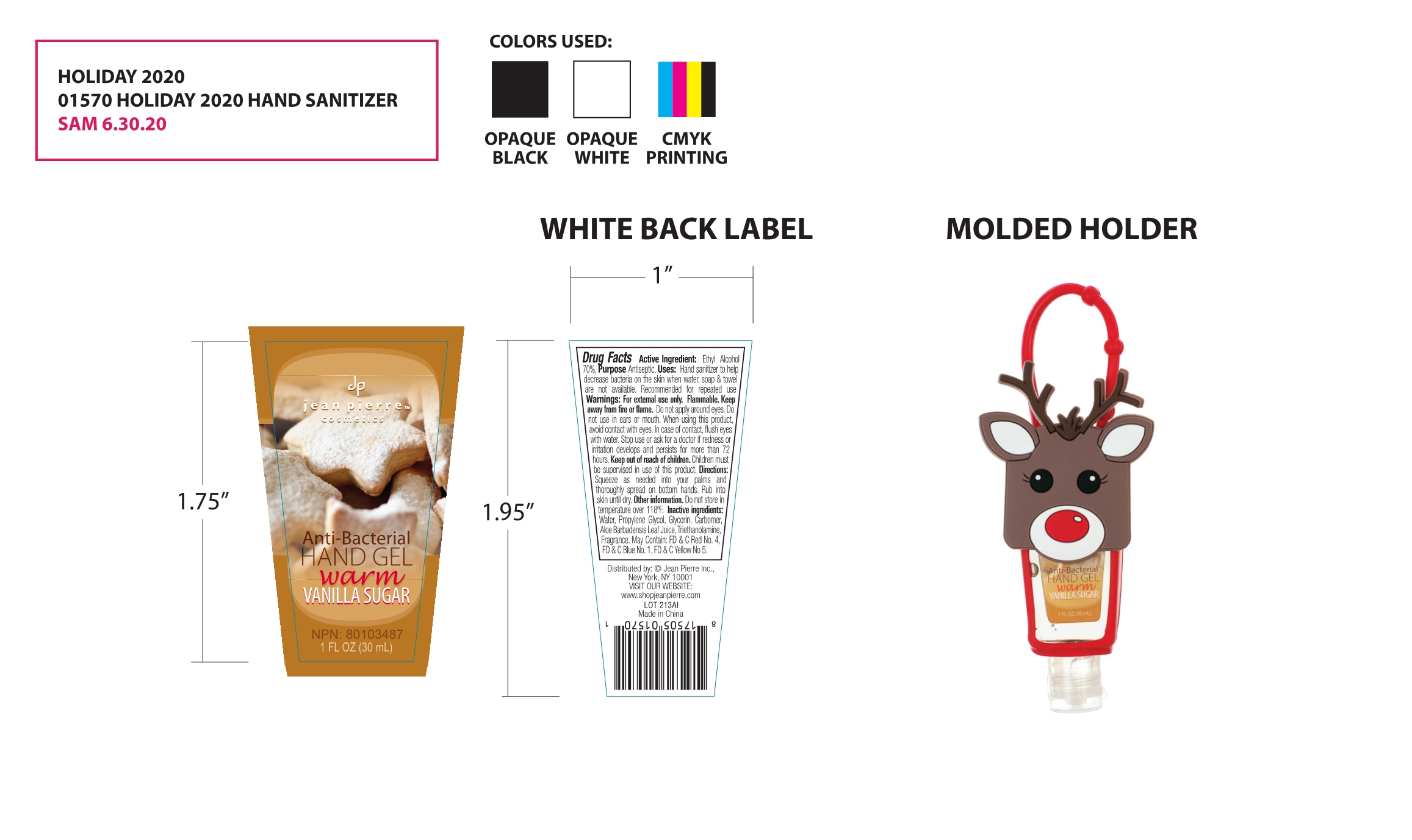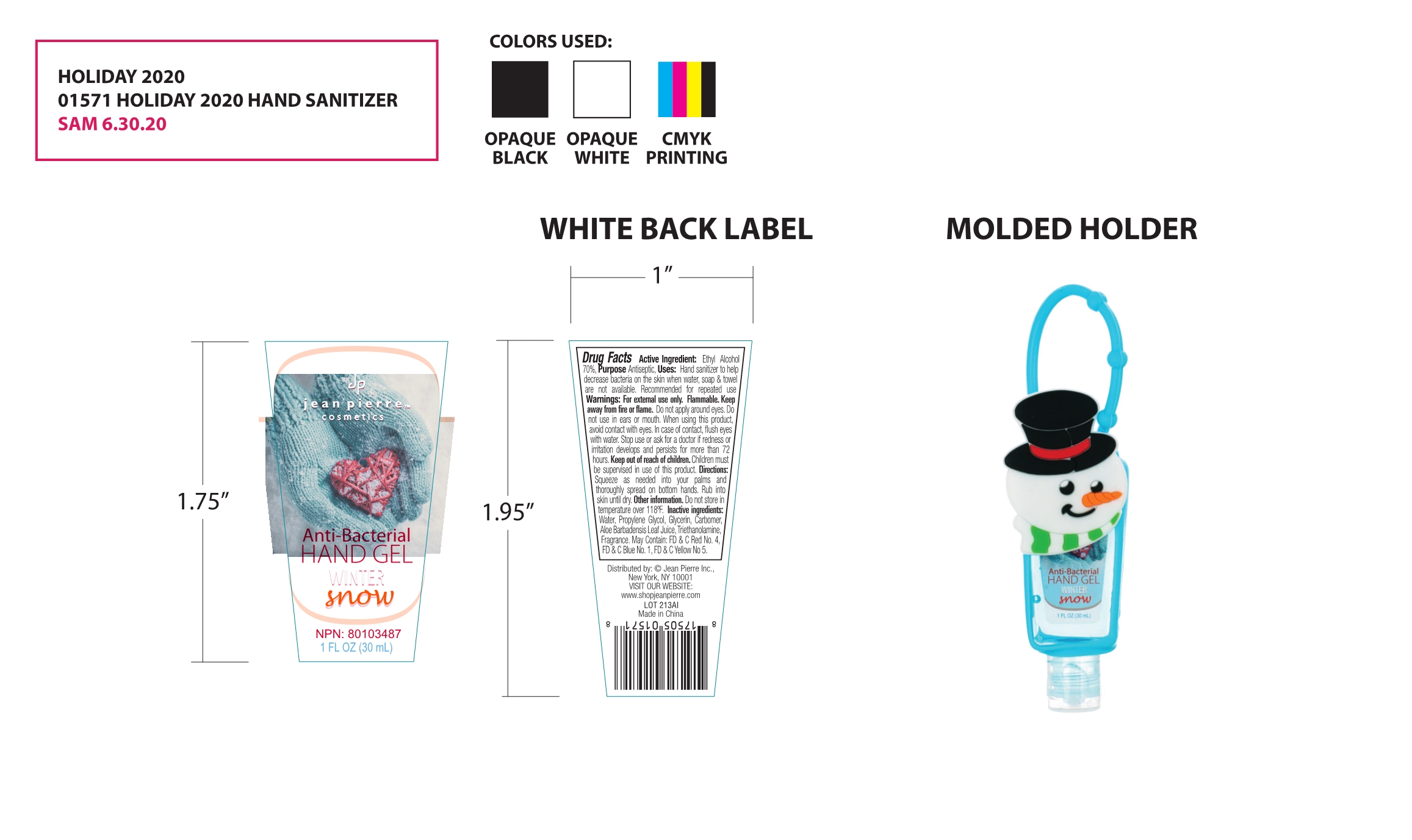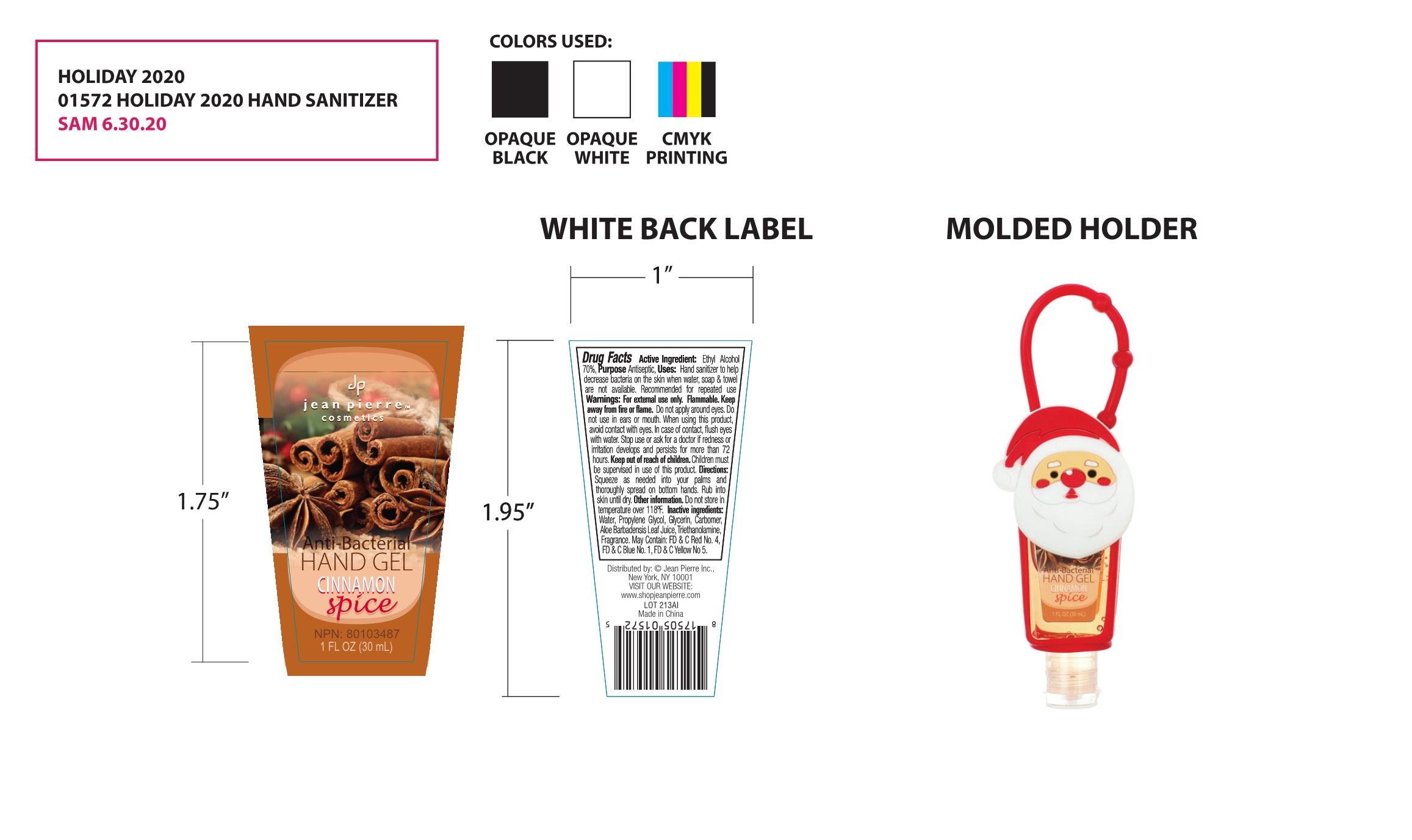 DRUG LABEL: hand gel
NDC: 79867-002 | Form: GEL
Manufacturer: Guangzhou meizi biotechnology co. LTD
Category: otc | Type: HUMAN OTC DRUG LABEL
Date: 20220330

ACTIVE INGREDIENTS: ALCOHOL 70 mL/100 mL
INACTIVE INGREDIENTS: CARBOMER HOMOPOLYMER, UNSPECIFIED TYPE; GLYCERIN; WATER; TROLAMINE; PROPYLENE GLYCOL; ALOE VERA LEAF

79867-002
hand gel

Active Ingredient(s)

Ethyl Alcohol 70%

Purpose

Antiseptic

Use

Hand sanitizer to help decrease bacteria on the skin when water, soap & towel are not available. Recommended for repeated use

Warnings

For external use only. Flammable. Keep away from fire or flame.

Do not apply around eyes. Do not use in ears or mouth.

When using this product, avoid contact with eyes. In case of contact, flush eyes with water.

Stop use or ask for a doctor if redness or irritation develops and persists for more than 72 hours.

Keep out of reach of children. Children must be supervised in use of this product.

Do not use

Do not apply around eyes. Do not use in ears or mouth.

When using this product, avoid contact with eyes. In case of contact, flush eyes with water.

Stop use or ask for a doctor if redness or irritation develops and persists for more than 72 hours.

Keep out of reach of children. Children must be supervised in use of this product.

Stop use or ask for a doctor if redness or irritation develops and persists for more than 72 hours.

Keep out of reach of children. Children must be supervised in use of this product.

Directions

Squeeze as needed into your palms and thoroughly spread on bottom hands. Rub into skin until dry.

Other information

Do not store in temperature over 118°F.

Inactive ingredients

Water, Propylene Glycol, Glycerin, Carbomer, Aloe Barbadensis Leaf Juice, Triethanolamine, Fragrance.
May Contain: FD & C Red No. 4, FD & C Blue No. 1, FD & C Yellow No 5.